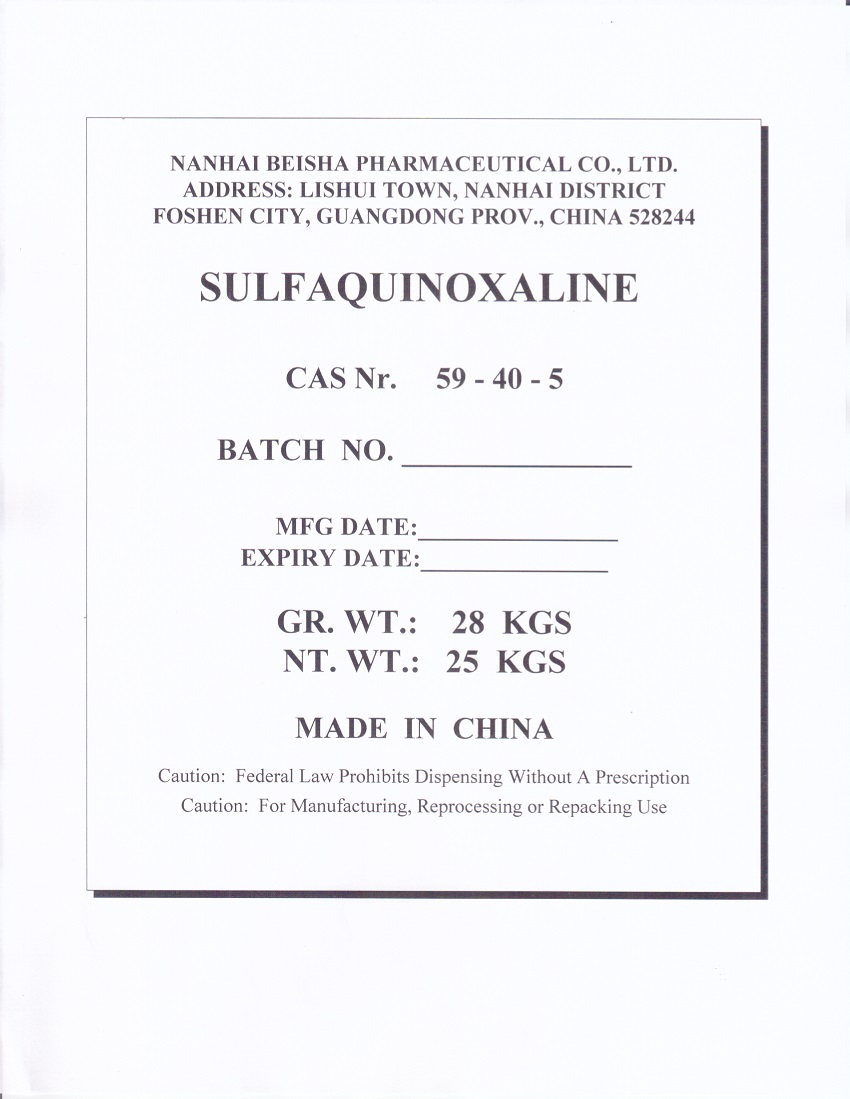 DRUG LABEL: SULFAQUINOXALINE
NDC: 63422-704 | Form: POWDER
Manufacturer: NANHAI BEISHA PHARMACEUTICAL CO., LTD.
Category: other | Type: BULK INGREDIENT - ANIMAL DRUG
Date: 20250825

ACTIVE INGREDIENTS: SULFAQUINOXALINE 1 kg/1 kg

PACKAGE LABEL

Add image transcription here...